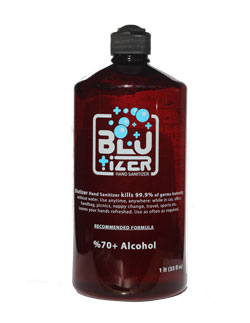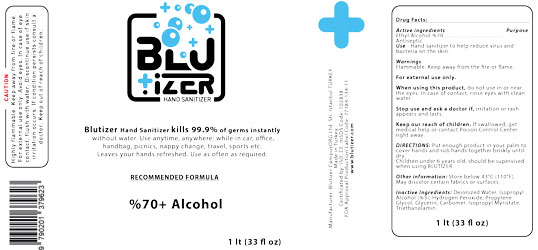 DRUG LABEL: Blutizer Hand Sanitizer Gel
NDC: 77184-135 | Form: SOLUTION, GEL FORMING, EXTENDED RELEASE
Manufacturer: CampusORG Turizm Organizasyon Reklamcilik Pazarlama Sanayi ve Ticaret Limited Sirketi
Category: otc | Type: HUMAN OTC DRUG LABEL
Date: 20200810

ACTIVE INGREDIENTS: ALCOHOL 70 mL/100 mL
INACTIVE INGREDIENTS: PROPYLENE GLYCOL 0.1 mL/100 mL; HYDROGEN PEROXIDE 0.125 mL/100 mL; ISOPROPYL MYRISTATE 0.02 mL/100 mL; ISOPROPYL ALCOHOL 3 mL/100 mL; CARBOMER 980 0.28 mL/100 mL; TROLAMINE 0.28 mL/100 mL; WATER; GLYCERIN 1.45 mL/100 mL

ACTIVE INGREDIENT

Alcohol %70 (%96,4 volume) v/v Purpose: Antiseptic

Purpose

Antiseptic: Hand Sanitizer

USE IN SPECIFIC POPULATIONS

Hand Sanitizer to help reduce bacteria that potentially can cause disease. For use when soap and water are not available.

Warnings

For external use only. Flammable. Keep away from heat of flame.

Do Not Use

in children less than 2 months of age.

on open skin wounds

When using this product keep out of eyes, ears, and mouth. In case of contact with eyes, rinse eyes thoroughly with warter.

Stop use and ask a doctor if irritation or rash occurs. These may be signs of a serious contiditon.

Keep our of reac of children. If swallowed, get medical help or contact a Poison Control Center right away.

Stop use and ask a doctor if irritation or rash occurs. These may be signs of a serious condition.

Keep out of reach of children. If swallowed, get medical help or contact a Poison Control Center right away.

DOSAGE AND ADMINISTRATION

Place enough product on hands to cover all surfaces. Rub hand together until dry.

Supervise children under 6 years of age when using this product to avoid swallowing.

STORAGE AND HANDLING

Store between 15-43C (59-110F)

Avoid freezing and excessive heat above 43C (110F)

INACTIVE INGREDIENT

- Isopropyl Alcohol %3 (Purpose: Antiseptic and Anti-Foaming)
- Glycerin (Purpose: Humidifier)
- Hydrogen Peroxide (Purpose: Sterilizing)
- Propylene Glycol
- Isopropyl Myristate
- Trolamine
- Carbomer
- Prufied Water USP (Purpose: Solvent)

PACKAGE LABEL

1000 mL (33 fl oz) NDC: 77184-135-11